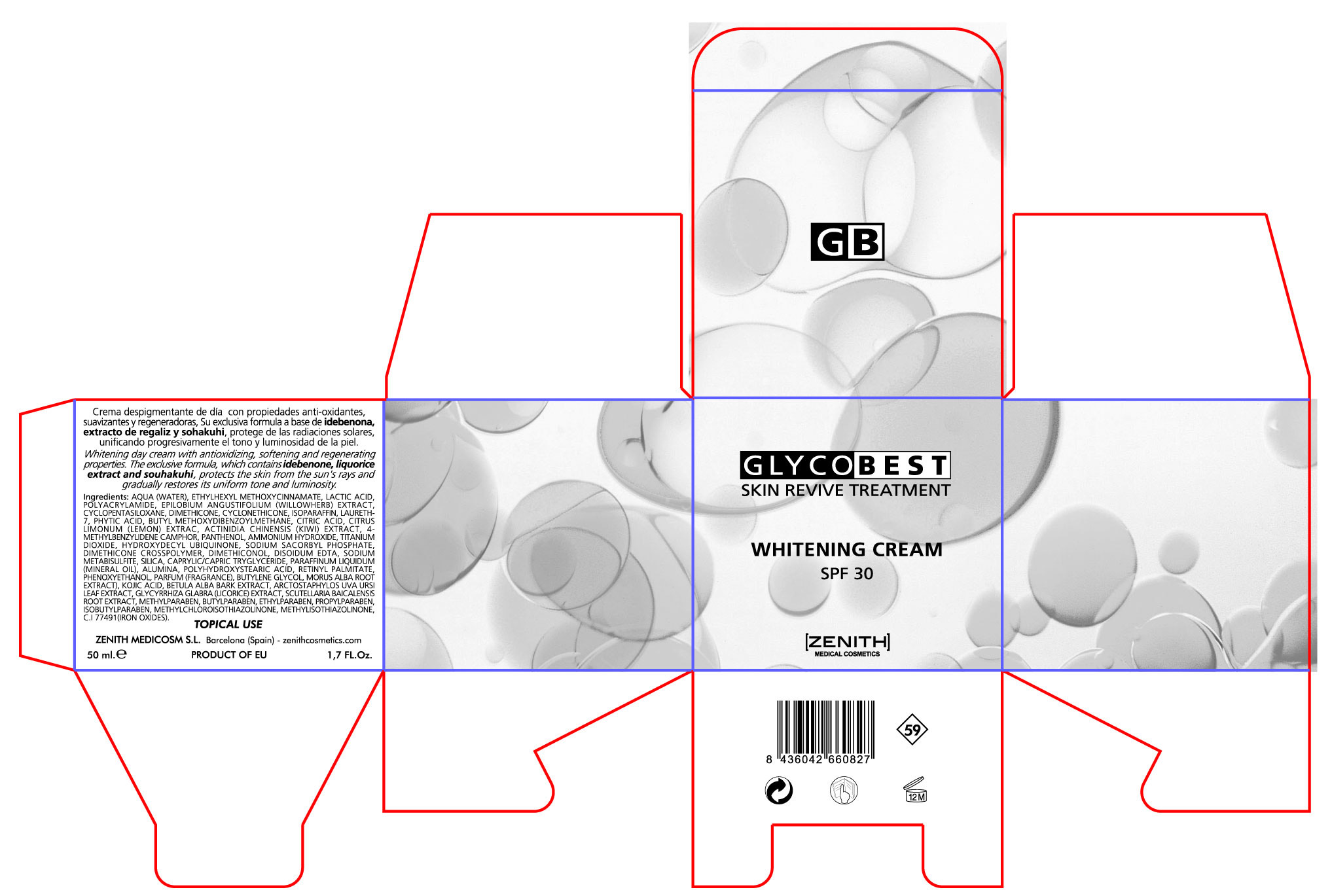 DRUG LABEL: Whitening
NDC: 42248-129 | Form: CREAM
Manufacturer: Zenith Medicosm SL
Category: otc | Type: HUMAN OTC DRUG LABEL
Date: 20120523

ACTIVE INGREDIENTS: OCTINOXATE 3.5 mL/50 mL; AVOBENZONE 1.5 mL/50 mL; TITANIUM DIOXIDE 12.5 mL/50 mL
INACTIVE INGREDIENTS: LACTIC ACID; PROPYLPARABEN; POLYACRYLAMIDE (1500 MW); CYCLOMETHICONE; ARCTOSTAPHYLOS UVA-URSI LEAF; LICORICE; WATER; EPILOBIUM ANGUSTIFOLIUM LEAF; LEMON JUICE; CYCLOMETHICONE 5; LAURETH-7; CITRIC ACID MONOHYDRATE; fytic acid; BUTYLENE GLYCOL; VITAMIN A PALMITATE; SCUTELLARIA BAICALENSIS ROOT; METHYLPARABEN; ENZACAMENE; BETULA PUBESCENS BARK; TRICLOSAN; EDETATE DISODIUM; DIMETHICONOL (41 MPA.S); POLYHYDROXYSTEARIC ACID (2300 MW); ETHYLPARABEN; BUTYLPARABEN; iSOBUTYLPARABEN; PANTHENOL; WHITE MULBERRY; SODIUM METABISULFITE; IDEBENONE; TRICAPRYLIN; KOJIC ACID; METHYLISOTHIAZOLINONE; METHYLCHLOROISOTHIAZOLINONE

Drug Facts

Active Ingredient

Octinoxate 7.5%

Titanium Oxide 25%

Avobenzone 3%

Description

A cream with high concentrations of Vitamin A, Vitamin C and marine collagen, which are particularly indicated for oily and aging skin. It combines the regenerating action of Retinol and the bateriostatic action of Vitamin C to fight premature skin aging. Softens and smoothes the skin, reduces wrinkles and gives the skin an even, radiant glow.

200ml. 6.8Fl.Oz.

Warning

TOPICAL USE